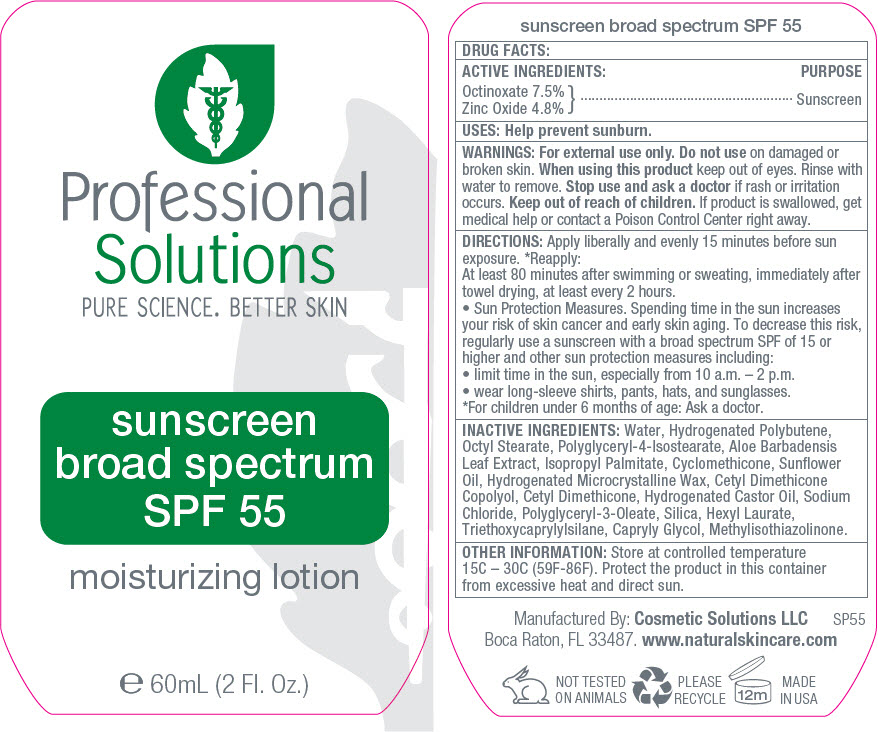 DRUG LABEL: Professional Solutions - Sunscreen Broad Spectrum SPF 55 Moisturizing
NDC: 66163-2616 | Form: CREAM
Manufacturer: Cosmetic Solutions LLC
Category: otc | Type: HUMAN OTC DRUG LABEL
Date: 20191016

ACTIVE INGREDIENTS: Octinoxate 75 mg/1 g; Zinc Oxide 48 mg/1 g
INACTIVE INGREDIENTS: Water; Isocetyl Stearate; Sorbitol; Cetostearyl Alcohol; Cyclomethicone 5; Glyceryl Monostearate; PEG-100 Stearate; Alcohol; Octisalate; Polyoxyl 20 Cetostearyl Ether; .Alpha.-Tocopherol Acetate; Vinylpyrrolidone/Eicosene Copolymer; Hydroxyethyl Acrylate/Sodium Acryloyldimethyl Taurate Copolymer (100000 MPA.S AT 1.5%); Ethylhexylglycerin; Betula Pubescens Bark; Garden Cress Sprout; Sage; Cola Acuminata Seed; Camellia Oleifera Leaf; Aloe Vera Leaf; Xanthan Gum; Isomalt; Edetate Disodium Anhydrous; Triethoxycaprylylsilane; Sodium Benzoate; Caprylyl Glycol; Phenoxyethanol

Professional Solutions - Sunscreen Broad Spectrum SPF 55 Moisturizing Lotion

DRUG FACTS

ACTIVE INGREDIENTS

Octinoxate 7.5%

Zinc Oxide 4.8%

PURPOSE

Sunscreen

USES

Help prevent sunburn.

WARNINGS

For external use only.

Do not use on damaged or broken skin.

When using this product keep out of eyes. Rinse with water to remove.

Stop use and ask a doctor if rash or irritation occurs.

Keep out of reach of children. If product is swallowed, get medical help or contact a Poison Control Center right away.

DIRECTIONS

Apply liberally and evenly 15 minutes before sun exposure. [For children under 6 months of age: Ask a doctor.] Reapply:

At least 80 minutes after swimming or sweating, immediately after towel drying, at least every 2 hours.

- Sun Protection Measures. Spending time in the sun increases your risk of skin cancer and early skin aging. To decrease this risk, regularly use a sunscreen with a broad spectrum SPF of 15 or higher and other sun protection measures including:
- limit time in the sun, especially from 10 a.m. – 2 p.m.
- wear long-sleeve shirts, pants, hats, and sunglasses.

INACTIVE INGREDIENTS

Water, Hydrogenated Polybutene, Octyl Stearate, Polyglyceryl-4-Isostearate, Aloe Barbadensis Leaf Extract, Isopropyl Palmitate, Cyclomethicone, Sunflower Oil, Hydrogenated Microcrystalline Wax, Cetyl Dimethicone Copolyol, Cetyl Dimethicone, Hydrogenated Castor Oil, Sodium Chloride, Polyglyceryl-3-Oleate, Silica, Hexyl Laurate, Triethoxycaprylylsilane, Capryly Glycol, Methylisothiazolinone.

OTHER INFORMATION

Store at controlled temperature 15C – 30C (59F-86F). Protect the product in this container from excessive heat and direct sun.

Manufactured By: Cosmetic Solutions LLC
Boca Raton, FL 33487.

PRINCIPAL DISPLAY PANEL - 60 mL Bottle Label

Professional
Solutions
PURE SCIENCE. BETTER SKIN

sunscreen
broad spectrum
SPF 55

moisturizing lotion

e 60mL (2 Fl. Oz.)